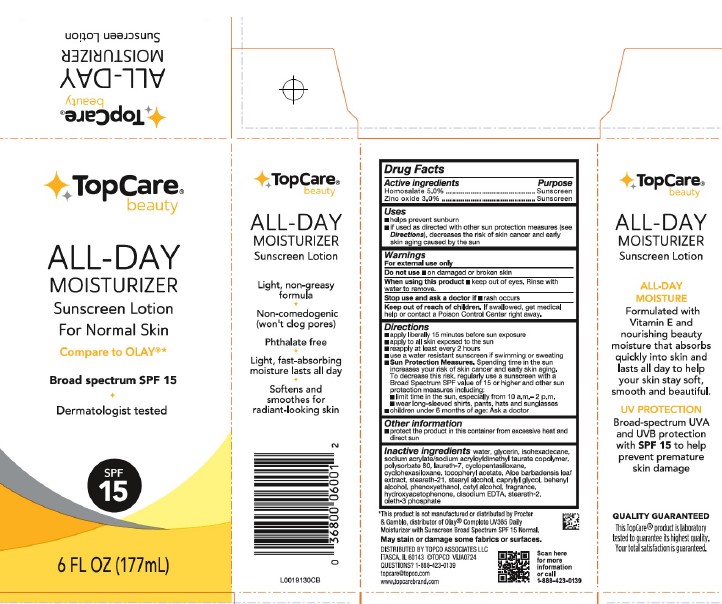 DRUG LABEL: Beauty Hydrating
NDC: 36800-513 | Form: LOTION
Manufacturer: Topco Associates LLC
Category: otc | Type: HUMAN OTC DRUG LABEL
Date: 20260213

ACTIVE INGREDIENTS: HOMOSALATE 50 mg/1 mL; ZINC OXIDE 30 mg/1 mL
INACTIVE INGREDIENTS: WATER; GLYCERIN; ISOHEXADECANE; SODIUM ACRYLATE/SODIUM ACRYLOYLDIMETHYLTAURATE COPOLYMER (4000000 MW); POLYSORBATE 80; LAURETH-7; CYCLOMETHICONE 5; CYCLOMETHICONE 6; .ALPHA.-TOCOPHEROL ACETATE; ALOE VERA LEAF; STEARETH-21; STEARYL ALCOHOL; CAPRYLYL GLYCOL; DOCOSANOL; PHENOXYETHANOL; CETYL ALCOHOL; HYDROXYACETOPHENONE; EDETATE DISODIUM; STEARETH-2; OLETH-3 PHOSPHATE

Top Care 043.000/043AA
Original Beauty Lotion SPF 15

Active ingredients

Homosalate 5.0%

Zinc oxide 3.0%

Purpose

Sunscreen

Uses

- helps prevent sunburn
- if used as directed with other sun protection measures (see Directions), decreases the risk of skin cancer and early skin aging caused by the sun

Warnings

For external use only

Do not use

on damaged or broken skin

when using this product

keep out of eyes. Rinse with water to remove.

Stop use and ask a doctor if

rash occurs

Keep out of reach of children

If swallowed, get medical help or contact a Poison Control Center right away.

Directions

- apply liberally 15 minutes before sun exposure
- apply to all skin exposed to the sun
- reapply at least every 2 hours
- use a water resistant sunscreen if swimming or sweating
- Sun Protection measures. Spending time in the sun increases your risk of skin cancer and early skin aging. To decrease this risk, regularly use a sunscreen with a Broad spectrum SPF value of 15 or higher and other sun protection measures including:
- limit the time in the sun, especially from 10 a.m. - 2 p.m.
- wear long-sleeved shirts, pants, hats and sunglasses
- children under 6 months of age: ask a doctor

Other information

- protect the product in this container from excessive heat and direct sun

Inactive ingredients

water, glycerin, isohexadecane, sodium acrylate/sodium acryloyldimethyl taurate copolymer, polysorbate 80, laureth-7, cyclopentasiloxane, cyclohexasiloxane, tocopheryl acetate, Aloe barbadensis leaf extract, steareth-21, stearyl alcohol, caprylyl glycol, behenyl alcohol, phenoxyethanol, cetyl alcohol, fragrance, hydroxyacetophenone, disodium EDTA, steareth-2, oleth-3 phosphate

Disclaimer

*This product is not manufactured or distributed by Procter & Gamble, distributor of Olay®Complete UV365 Daily Moisturizer with Sunscreen Broad Spectrum SPF 15 Normal.

May stain or damage some fabrics or surfaces.

Adverse Reactions

DISTRIBUTED BY TOPCO ASSOCIATES LLC

ITASCA, IL 60143 © TOPCO VIJA0724

QUESTIONS? 1-888-423-0139

topcare@topco.com

www.topcarebrand.com

Scan here for more information or call 1-888-423-0139

principal display panel - side panels

Top Care®beauty

ALL-DAY MOISTURIZER

Sunscreen Lotion

ALL-DAY MOISTURE

Formulated with Vitamin E and nourishing beauty moisture that absorbs quickly into skin and lasts all day to help your skin stay soft, smooth and beautiful.

UV PROTECTION

Broad-spetrum UVA and UVB protection with SPF 15 to help prevent premature skin damage

QUALITY GUARANTEED

This TopCare®product is laboratory tested to guarantee its highest quality. Your total satisfaction is guaranteed.

Top Care®beauty

ALL-DAY MOISTURIZER

Sunscreen Lotion

Light, non-greasy formula

Non-comedogenic (won't clog pores)

Phthalate free

Light, fast absorbing moisture lasts all day

Softens and smoothes for radiant-looking skin

principal display panel

Top Care®beauty

ALL-DAY MOISTURIZER

Sunscreen Lotion

For Normal Skin

Compare to OLAY®*

Broad spectrum SPF 15

Dermatologist tested

SPF 15

6 FL OZ (177 mL)